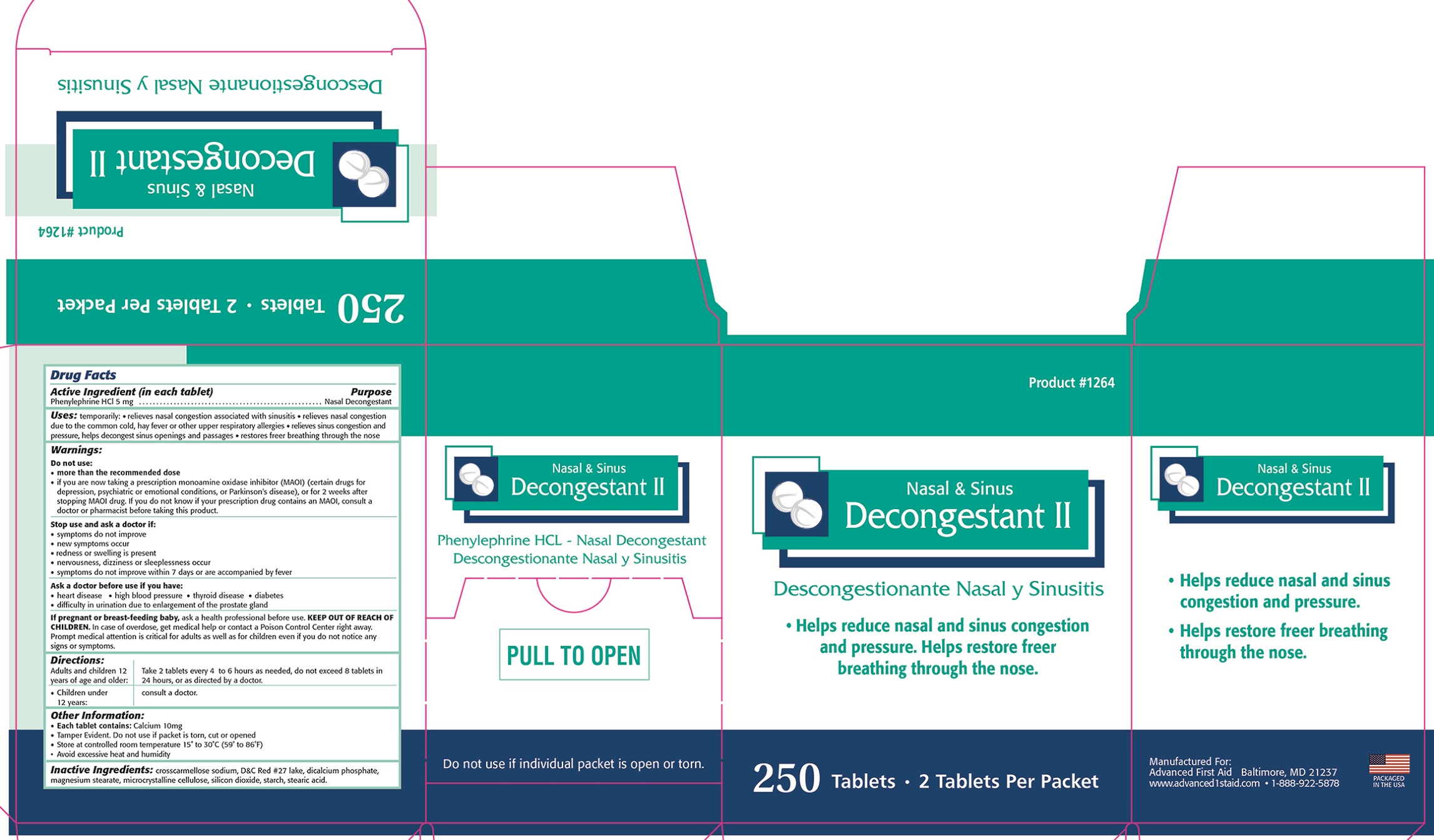 DRUG LABEL: DECONGESTANT II
NDC: 67060-333 | Form: TABLET
Manufacturer: ADVANCED FIRST AID, INC.
Category: otc | Type: HUMAN OTC DRUG LABEL
Date: 20190807

ACTIVE INGREDIENTS: PHENYLEPHRINE HYDROCHLORIDE 5 1/1 1
INACTIVE INGREDIENTS: CROSCARMELLOSE SODIUM; D&C RED NO. 27 ALUMINUM LAKE; CALCIUM PHOSPHATE, DIBASIC, DIHYDRATE; MAGNESIUM STEARATE; CELLULOSE, MICROCRYSTALLINE; SILICON DIOXIDE; STARCH, CORN; STEARIC ACID

ACTIVE INGREDIENT (IN EACH TABLET)- Phenylephrine HCl 5 mg

PURPOSE

Nasal Decongestant

INDICATIONS AND USAGE

Uses: temporarily: • relieves nasal congestion associated with sinusitis •relieves nasal congestion due to the common cold, hay fever or other upper respiratory allergies • relieves sinus congestion and pressure, helps decongest sinus openings and passages • restores freer breathing through the nose

Warnings:

Do not use: • more than the recommended dose

• if you are now taking a prescription monoamine oxidase inhibitor (MAOI) (certain drugs for depression, psychiatric or emotional conditions, or Parkinson's disease), or for 2 weeks after stopping MAOI drug. If you do not know if your prescription drug contains an MAOI, consult a doctor or pharmacist before taking this product.

Stop use and ask a doctor if:

• symptoms do not improve

• new symptoms occur

• redness or swelling is present

• nervousness, dizziness or sleeplessness occur

• symptoms do not improve within 7 days or are accompanied by fever

Ask a doctor before use if you have: • heart disease • high blood pressure • thyroid disease • diabetes • difficulty in urination due to enlargement of the prostate gland

PREGNANCY OR BREAST FEEDING

If pregnant or breast-feeding baby, ask a health professional before use.

KEEP OUT OF REACH OF CHILDREN. In case of overdose, get medical help or contact a Poison Control Center right away. Prompt medical attention is critical for adults as well as for children even if you do not notice any signs or symptoms.

Directions:

Adults and children 12 years of age and older: Take 2 tablets every 4 to 6 hours or as needed, do not exceed 8 tablets in 24 hours, or as directed by a doctor.

Children under 12 years: Consult a doctor.

INACTIVE INGREDIENT

Inactive Ingredients: crosscarmellose sodium, D&C Red #27 lake, dicalcium phosphate, magnesium stearate, microcrystalline cellulose, silicon dioxide, starch, stearic acid